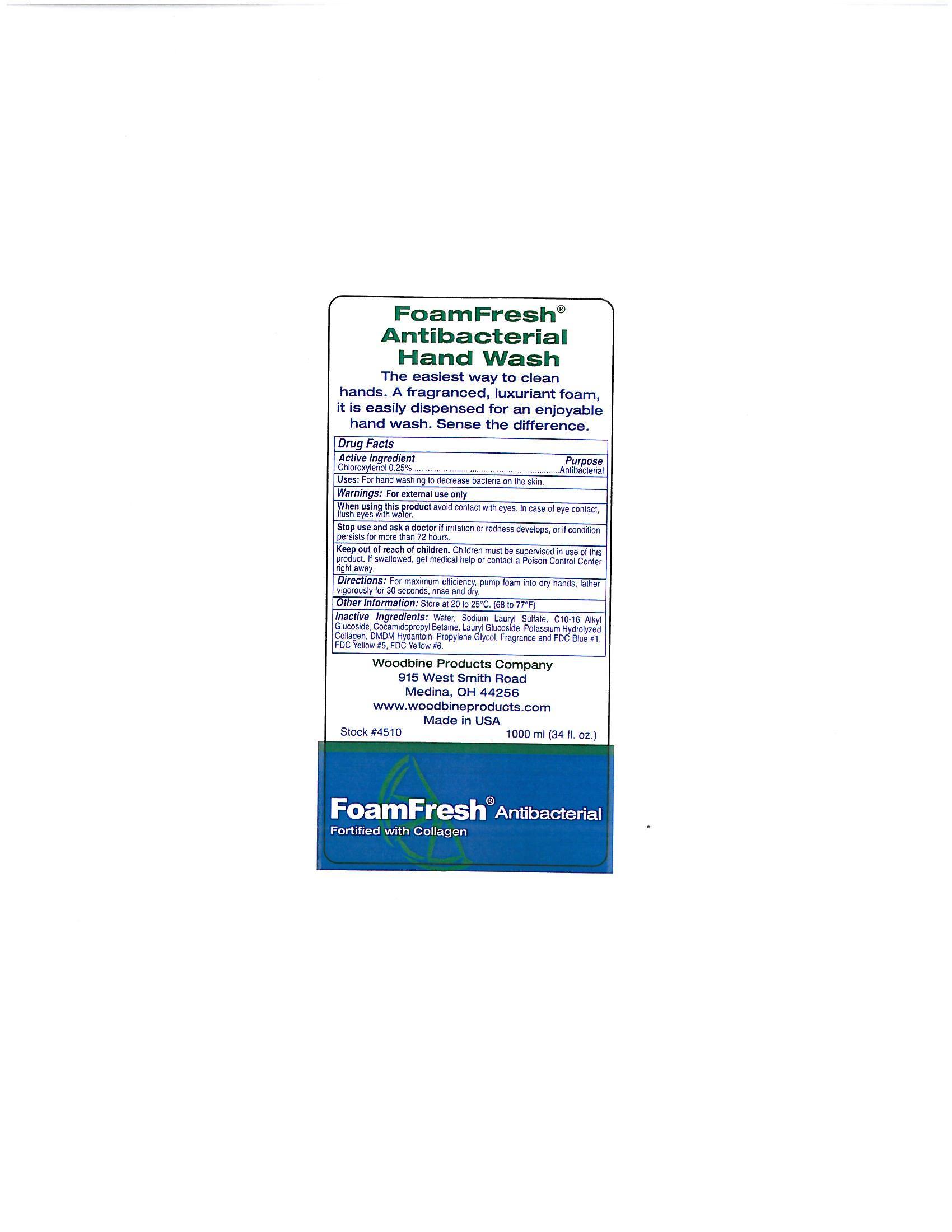 DRUG LABEL: FoamFresh Antibacterial Hand Wash
NDC: 11429-1005 | Form: LIQUID
Manufacturer: Woodbine Products Company
Category: otc | Type: HUMAN OTC DRUG LABEL
Date: 20250617

ACTIVE INGREDIENTS: CHLOROXYLENOL 2.5 mg/1 mL
INACTIVE INGREDIENTS: WATER; SODIUM LAURYL SULFATE; COCAMIDOPROPYL BETAINE; LAURYL GLUCOSIDE; DMDM HYDANTOIN; PROPYLENE GLYCOL; FD&C BLUE NO. 1; FD&C YELLOW NO. 6; FD&C YELLOW NO. 5

Drug Facts 11429-1005

Active Ingredient

Chloroxylenol 0.25%

Purpose

Antibacterial

Uses:

For hand washing to decrease bacteria on the skin.

Warnings:

For external use only

When using this product avoid contact with eyes.

In case of eye contact, flush eyes with water.

Stop use and ask a doctor if irritation or redness develops, or if condition persists for more than 72 hours.

Keep out of reach of children.

Children must be supervised in use of this product.

If swallowed, get medical help or contact a Poison Control Center right away.

Directions:

For maximum efficiency, pump foam into dry hands, lather vigorously for 30 seconds, rinse and dry.

Other Information:

Store at 20 to 25 C. (68 to 77 F)

Inactive Ingredient:

Water, Sodium Lauryl Sulfate, C10-16 Alkyl Glucoside, Cocamidopropyl Betaine, Lauryl Glucoside, Potassium Hydrolyzed Collagen, DMDM Hydantoin, Propylene Glycol, Fragrance and FDC Blue #1, FDC Yellow #5, FDC Yellow #6.

PACKAGE LABEL

FoamFresh

Antibacterial Hand Wash

The easiest way to clean

hands. A fragranced, luxuriant foam,

it is easily dispensed for an enjoyable

hand wash. Sense the difference.

Woodbine Products Company

915 West Smith Road

Medina, OH 44256

www.woodbineproducts.com

Made in USA

Stock #4510 1000 ml. (34 fl. oz.)

FoamFresh Antibacterial

Fortified with Collagen